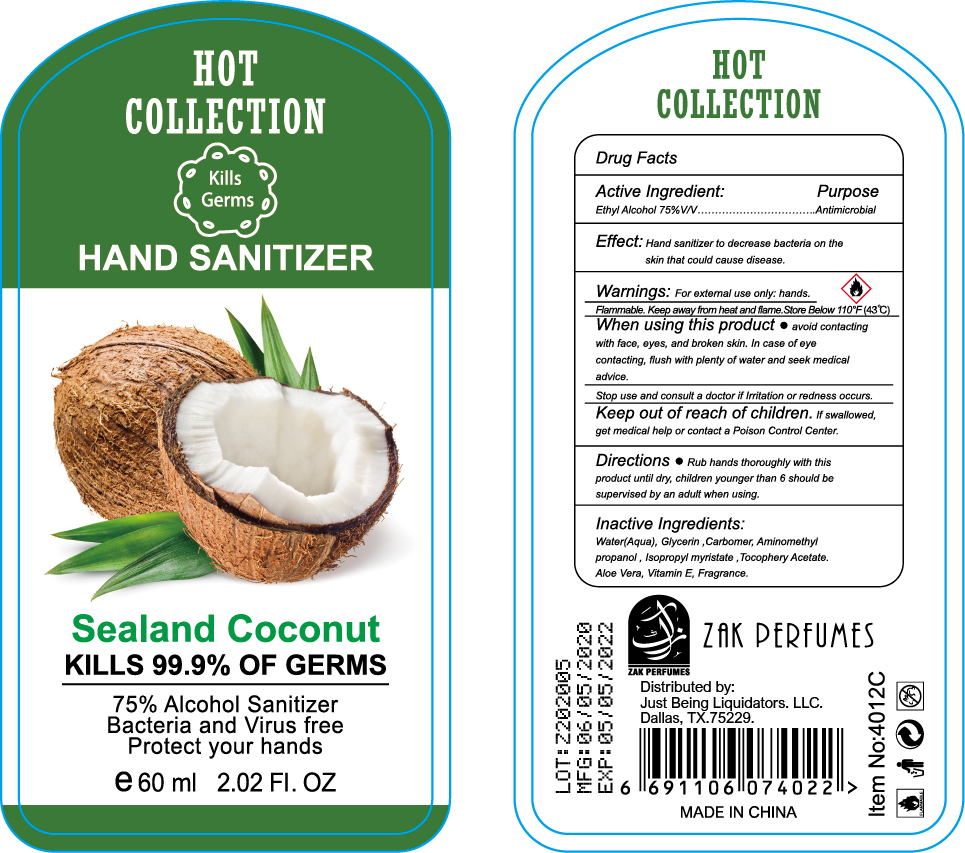 DRUG LABEL: HOT COLLECTION HAND SANITIZER Sealand Coconut
NDC: 78408-002 | Form: SOLUTION
Manufacturer: JINHUA VENICE COSMETIC CO., LTD
Category: otc | Type: HUMAN OTC DRUG LABEL
Date: 20200526

ACTIVE INGREDIENTS: ALCOHOL 75 mL/100 mL
INACTIVE INGREDIENTS: WATER; GLYCERIN; ALOE VERA WHOLE; .ALPHA.-TOCOPHEROL ACETATE; CARBOMER 940; AMINOMETHYL PROPANEDIOL; ISOPROPYL MYRISTATE

NA

Active Ingredient(s)

Ethyl Alcohol 75% v/v

Purpose

Antimicrobial

Use

Hand sanitizer to decrease bacteria on the skin that could cause disease

Warnings

For external use only.

Flammable. Keep away from heat and flame

When using this product keep out of eyes, ears, and mouth. In case of eye contact, flush with plenty of water and seek medical advice

Stop use and consult a doctor if irritation or redness occurs

Keep out of reach of children. if swallowed, get medical help or contact a Poison Control Center

Directions

Rub hands thoroughly with this product untill dry

Children younger than 6 should be supervised by an adult when using

Other information

Store below 110F (43C)

Inactive ingredients

Water, glycerin, carbomer, aminomethyl propanol, isopropyl myristate, tocopheryl acetate, aloe vera, fragrance